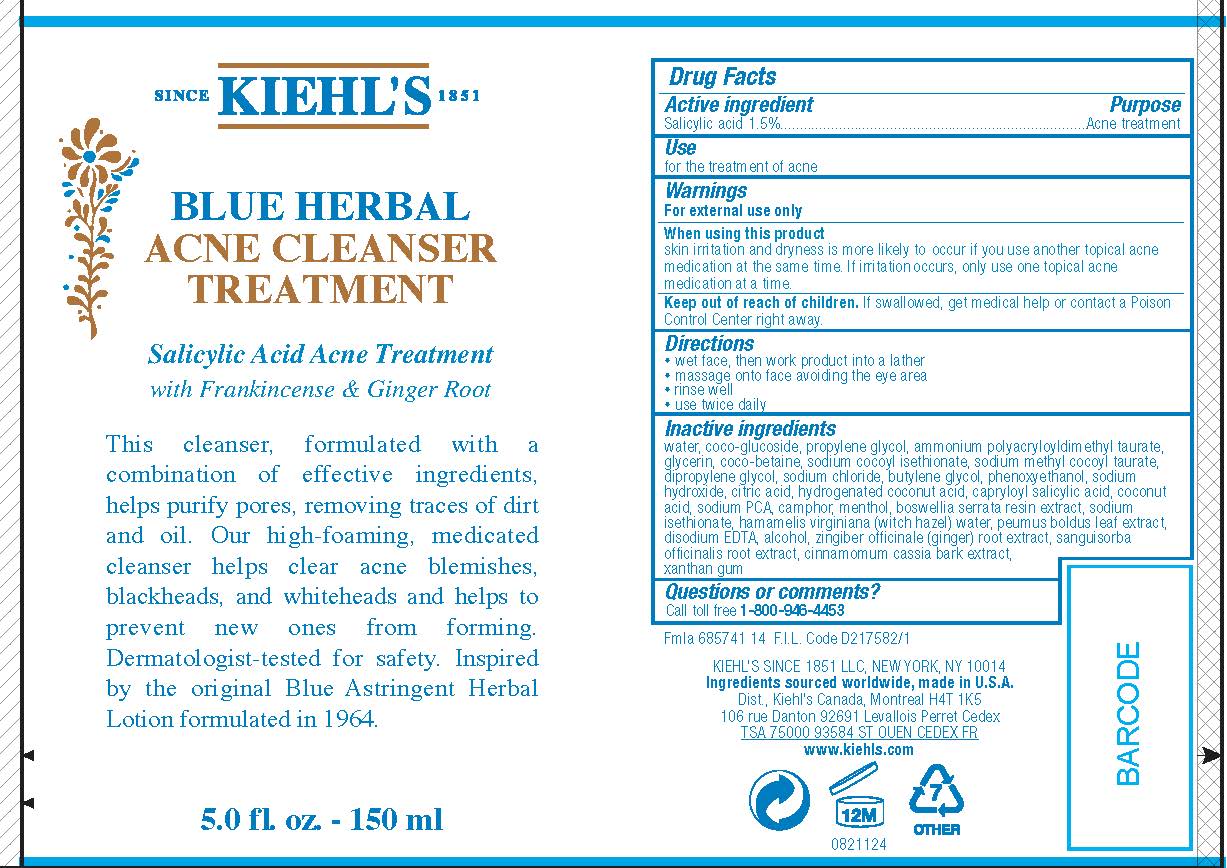 DRUG LABEL: Kiehls Since 1851 Blue Herbal Acne Cleanser Treatment
NDC: 49967-618 | Form: LOTION
Manufacturer: L'Oreal USA Products Inc
Category: otc | Type: HUMAN OTC DRUG LABEL
Date: 20231230

ACTIVE INGREDIENTS: SALICYLIC ACID 15 mg/1 mL
INACTIVE INGREDIENTS: WATER; COCO GLUCOSIDE; PROPYLENE GLYCOL; GLYCERIN; COCO-BETAINE; SODIUM COCOYL ISETHIONATE; SODIUM METHYL COCOYL TAURATE; DIPROPYLENE GLYCOL; SODIUM CHLORIDE; BUTYLENE GLYCOL; PHENOXYETHANOL; SODIUM HYDROXIDE; CITRIC ACID MONOHYDRATE; HYDROGENATED COCONUT OIL; CAPRYLOYL SALICYLIC ACID; COCONUT ACID; SODIUM PYRROLIDONE CARBOXYLATE; CAMPHOR (SYNTHETIC); MENTHOL; INDIAN FRANKINCENSE; SODIUM ISETHIONATE; HAMAMELIS VIRGINIANA TOP WATER; PEUMUS BOLDUS LEAF; EDETATE DISODIUM; ALCOHOL; GINGER; SANGUISORBA OFFICINALIS ROOT; CHINESE CINNAMON; XANTHAN GUM

Drug Facts

Active ingredient

Salicylic acid 1.5%

Purpose

Acne treatment

Use

for the treatment of acne

Warnings

For external use only

When using this product

skin irritation and dryness is more likely to occur if you use another topical acne medication at the same time. If irritation occurs, only use one topical acne medication at a time.

Keep out of reach of children.

If swallowed, get medical help or contact a Poison Control Center right away.

Directions

- wet face, then work product into a lather
- massage onto face avoiding the eye area
- rinse well
- use twice daily

Inactive ingredients

water, coco-glucoside, propylene glycol, ammonium polyacryloyldimethyl taurate, glycerin, coco-betaine, sodium cocoyl isethionate, sodium methyl cocoyl taurate, dipropylene glycol, sodium chloride, butylene glycol, phenoxyethanol, sodium hydroxide, citric acid, hydrogenated coconut acid, capryloyl salicylic acid, coconut acid, sodium PCA, camphor, menthol, boswellia serrata resin extract, sodium isethionate, hamamelis virginiana (witch hazel) water, peumus boldus leaf extract, disodium EDTA, alcohol, zingiber officinale (ginger) root extract, sanguisorba officinalis root extract, cinnamomum cassia bark extract, xanthan gum

Questions or comments?

Call toll free 1-800-946-4453